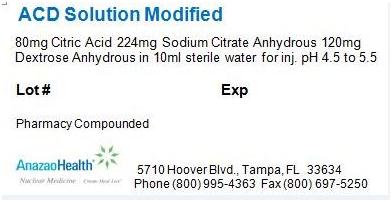 DRUG LABEL: ACD Solution Modified
NDC: 51808-201 | Form: SOLUTION
Manufacturer: AnazaoHealth Corporation
Category: prescription | Type: HUMAN PRESCRIPTION DRUG LABEL
Date: 20120523

ACTIVE INGREDIENTS: ANHYDROUS CITRIC ACID 8 mg/1 mL
INACTIVE INGREDIENTS: ANHYDROUS TRISODIUM CITRATE 22.4 mg/1 mL; ANHYDROUS DEXTROSE 12 mg/1 mL

ACD SOLUTION MODIFIED

Per your order, we have compounded ACD Solution Modified as a solution of 10 mL in a 100 mL vial. The characteristics of this compounded preparation are as follows

DESCRIPTION

Each 100 mL vial contains 80 mg citric acid, 224 mg sodium citrate anhydrous, and 120 mg dextrose anhydrous in a sterile, non-pyrogenic solution of 10 mL. The pH of the solution has been adjusted to be between 4.5 to 5.5

CLINICAL PHARMACOLOGY

In vitro, citrate ions combine with ionic calcium in the blood and the resulting

lack of ionic calcium prevents coagulation. Blood that has been treated with citrate anticoagulants is nontoxic to the body when injected in small amounts intravenously. After injection, citrate ions are rapidly removed from the blood by the liver, polymerized into glucose, and then metabolized in the usual manner

INDICATIONS AND USAGE

ACD solution modified is to be used in the labeling of red blood cells for intravenous administration with Cr-51 Sodium Chromate.

CONTRAINDICATIONS

There are no known contraindications.

DOSAGE AND ADMINISTRATION

Red Blood Cell Labeling Procedure

1. Labeling may be performed without washing or centrifugation steps directly in the reaction vial.
2. A 30 to 50 mL sample of whole blood is withdrawn from the patient and added aseptically to a vial of ACD Solution Modified.
3. 50 to 150 microcuries of Sodium Chromate 51 is then injected into the reaction vial using a shielded syringe. The amount of radioactivity added to the vial will
  depend on the intended use of the labeled red blood cells.
4. The suspension is incubated for 30 to 60 minutes at room temperature with frequent, gentle agitation.
5. After incubation, 100 mg Ascorbic Acid Injection is injected into the vial. The ascorbic acid reduces any remaining unbound dianionic chromium 51 to the anionic state which does not penetrate red blood cells; thus in vivo labeling of red blood cells is prevented.

Storage and Handling

Store the product at room temperature

PACKAGE LABEL.PRINCIPAL DISPLAY PANEL

Figure 1